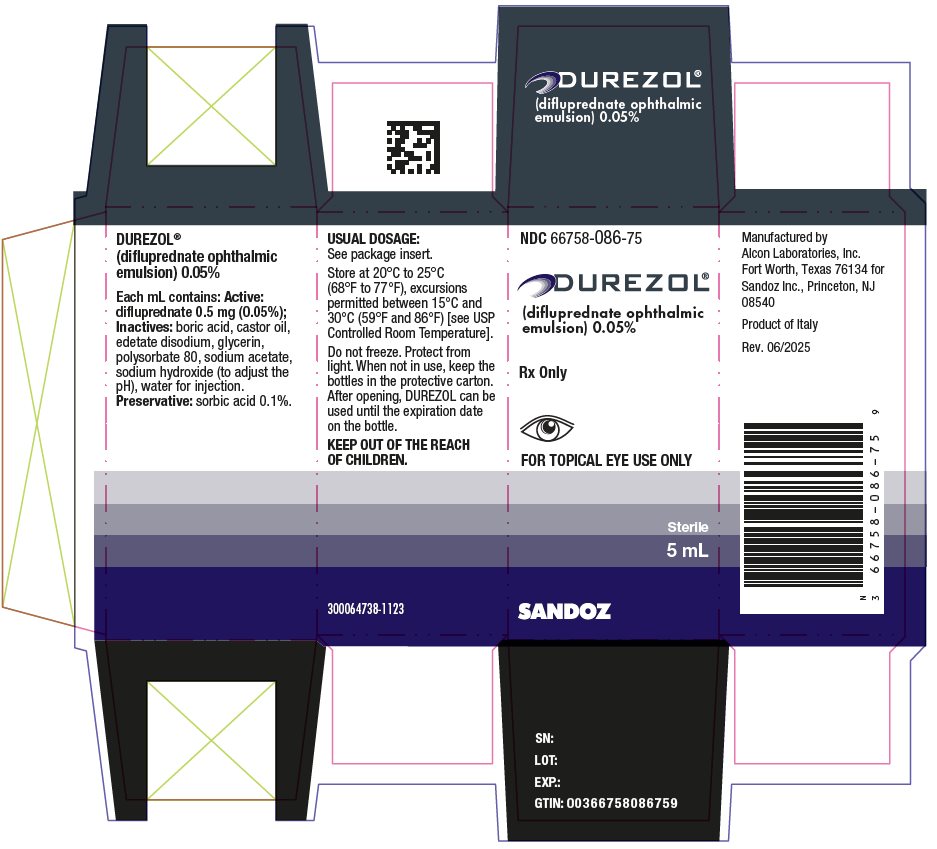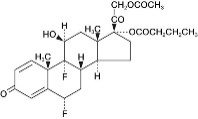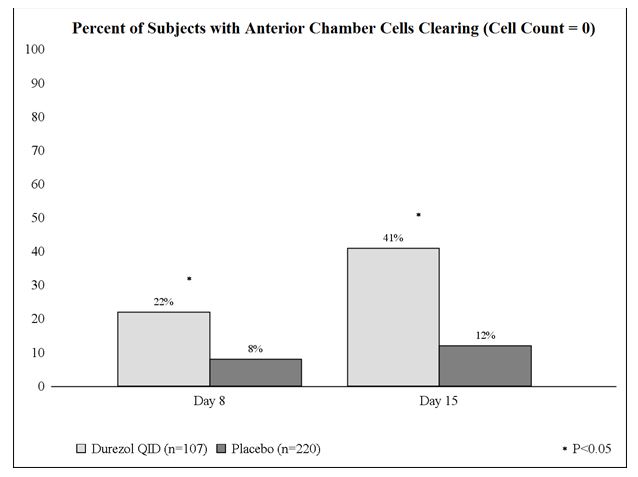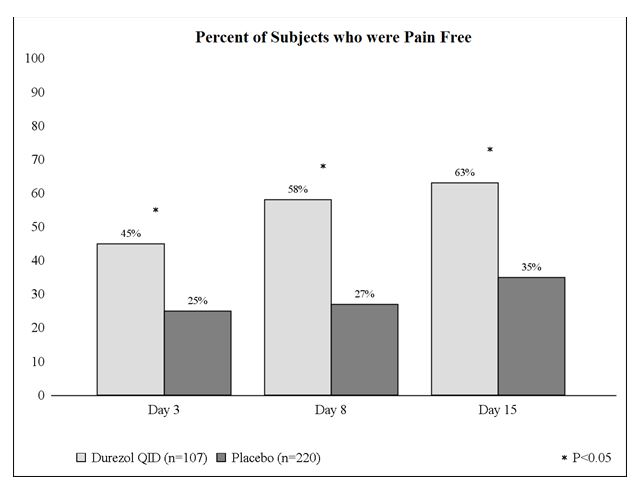 DRUG LABEL: DUREZOL
NDC: 66758-086 | Form: EMULSION
Manufacturer: Sandoz Inc
Category: prescription | Type: HUMAN PRESCRIPTION DRUG LABEL
Date: 20251024

ACTIVE INGREDIENTS: DIFLUPREDNATE 0.5 mg/1 mL
INACTIVE INGREDIENTS: BORIC ACID; CASTOR OIL; GLYCERIN; POLYSORBATE 80; WATER; SODIUM ACETATE; SODIUM HYDROXIDE; EDETATE DISODIUM; SORBIC ACID

HIGHLIGHTS OF PRESCRIBING INFORMATION

These highlights do not include all the information needed to use DUREZOL safely and effectively. See full prescribing information for DUREZOL.
DUREZOL® (difluprednate ophthalmic emulsion) 0.05%, for topical ophthalmic use
Initial U.S. Approval: 2008

1 INDICATIONS AND USAGE

DUREZOL® is a corticosteroid indicated for:

- The treatment of inflammation and pain associated with ocular surgery. (1.1)
- The treatment of endogenous anterior uveitis. (1.2)

2 DOSAGE AND ADMINISTRATION

- For the treatment of inflammation and pain associated with ocular surgery, instill one drop into the conjunctival sac of the affected eye 4 times daily beginning 24 hours after surgery and continuing throughout the first 2 weeks of the postoperative period, followed by 2 times daily for a week and then a taper based on the response. (2.1)
- For the treatment of endogenous anterior uveitis instill one drop into the conjunctival sac of the affected eye 4 times daily for 14 days followed by tapering as clinically indicated. (2.2)

3 DOSAGE FORMS AND STRENGTHS

Ophthalmic emulsion: 0.05%. (3)

4 CONTRAINDICATIONS

DUREZOL is contraindicated in most active viral diseases of the cornea and conjunctiva, including epithelial herpes simplex keratitis (dendritic keratitis), vaccinia, and varicella, and also in mycobacterial infection of the eye and fungal diseases of ocular structures. (4)

5 WARNINGS AND PRECAUTIONS

- Intraocular Pressure (IOP) Increase: Prolonged use of corticosteroids may result in glaucoma with damage to the optic nerve, defects in visual acuity and fields of vision. If DUREZOL is used for 10 days or longer, IOP should be monitored. (5.1)
- Cataracts: Use of corticosteroids may result in posterior subcapsular cataract formation. (5.2)
- Delayed Healing: The use of corticosteroids after cataract surgery may delay healing and increase the incidence of bleb formation. (5.3)
- Corneal and Scleral Melting: In those diseases causing thinning of the cornea or sclera, perforations have been known to occur with the use of topical corticosteroids. (5.4)
- Bacterial Infections: Prolonged use of corticosteroids may suppress the host response and thus increase the hazard of secondary ocular infections. In acute purulent conditions, corticosteroids may mask infection or enhance existing infection. If signs and symptoms fail to improve after 2 days, the patient should be reevaluated. (5.5)
- Viral Infections: Employment of a corticosteroid medication in the treatment of patients with a history of herpes simplex requires great caution. Use of ocular corticosteroids may prolong the course and may exacerbate the severity of many viral infections of the eye (including herpes simplex). (5.6)
- Fungal Infections: Fungal infections of the cornea are particularly prone to develop coincidentally with long-term local corticosteroid application. Fungus invasion must be considered in any persistent corneal ulceration where a corticosteroid has been used or is in use. (5.7)

6 ADVERSE REACTIONS

For treatment of inflammation and pain associated with ocular surgery, most common adverse reactions (incidence 5% to 15%) are corneal edema, ciliary and conjunctival hyperemia, eye pain, photophobia, posterior capsule opacification, anterior chamber cells, anterior chamber flare, conjunctival edema, and blepharitis.

For treatment of endogenous anterior uveitis, most common adverse reactions (incidence 5% to 10%) are blurred vision, eye irritation, eye pain, headache, increased IOP, iritis, limbal and conjunctival hyperemia, punctate keratitis, and uveitis.

To report SUSPECTED ADVERSE REACTIONS, contact Sandoz Inc., at 1-800-525-8747 or FDA at 1-800-FDA-1088 or www.fda.gov/medwatch.

FULL PRESCRIBING INFORMATION

1 INDICATIONS AND USAGE

1.1 Ocular Surgery

DUREZOL is indicated for the treatment of inflammation and pain associated with ocular surgery.

1.2 Endogenous Anterior Uveitis

DUREZOL is indicated for the treatment of endogenous anterior uveitis.

2 DOSAGE AND ADMINISTRATION

2.1 Ocular Surgery

Instill one drop into the conjunctival sac of the affected eye 4 times daily beginning 24 hours after surgery and continuing throughout the first 2 weeks of the postoperative period, followed by 2 times daily for a week and then a taper based on the response.

2.2 Endogenous Anterior Uveitis

Instill one drop into the conjunctival sac of the affected eye 4 times daily for 14 days followed by tapering as clinically indicated.

2.3 Prescribing Guidelines

The initial prescription and renewal of the medication order beyond one bottle should be made by a physician only after examination of the patient with the aid of magnification, such as slit lamp biomicroscopy, and where appropriate, fluorescein staining. If signs and symptoms fail to improve after two days, the patient should be reevaluated.

Not more than one bottle should be prescribed initially, and the prescription should not be refilled without further evaluation.

3 DOSAGE FORMS AND STRENGTHS

Ophthalmic emulsion containing 0.05% difluprednate.

4 CONTRAINDICATIONS

DUREZOL, as with other ophthalmic corticosteroids, is contraindicated in most active viral diseases of the cornea and conjunctiva, including epithelial herpes simplex keratitis (dendritic keratitis), vaccinia, and varicella, and also in mycobacterial infection of the eye and fungal disease of ocular structures.

5 WARNINGS AND PRECAUTIONS

5.1 Intraocular Pressure (IOP) Increase

Prolonged use of corticosteroids may result in glaucoma with damage to the optic nerve, defects in visual acuity and fields of vision. Corticosteroids should be used with caution in the presence of glaucoma. If DUREZOL is used for 10 days or longer, IOP should be routinely monitored.

5.2 Cataracts

The use of corticosteroids may result in posterior subcapsular cataract formation.

5.3 Delayed Healing

The use of corticosteroids after cataract surgery may delay healing and increase the incidence of bleb formation. In those diseases causing thinning of the cornea or sclera, perforations have been known to occur with the use of topical steroids. The initial prescription and renewal of the medication order beyond 28 days should be made by a physician only after examination of the patient with the aid of magnification, such as slit lamp biomicroscopy, and where appropriate, fluorescein staining.

5.4 Corneal and Scleral Melting

Various ocular diseases and long-term use of topical corticosteroids have been known to cause corneal and scleral thinning. Use of topical corticosteroids in the presence of thin corneal or scleral tissue may lead to perforation of the globe.

5.5 Bacterial Infections

Prolonged use of corticosteroids may suppress the host response and thus increase the hazard of secondary ocular infections. In acute purulent conditions, corticosteroids may mask infection or enhance existing infection. If signs and symptoms fail to improve after 2 days, the patient should be reevaluated.

5.6 Viral Infections

Use of ocular corticosteroids may prolong the course and may exacerbate the severity of many viral infections of the eye (including herpes simplex). Employment of a corticosteroid medication in the treatment of patients with a history of herpes simplex requires great caution; frequent slit lamp microscopy is recommended.

5.7 Fungal Infections

Fungal infections of the cornea are particularly prone to develop coincidentally with long-term local corticosteroid application. Fungus invasion must be considered in any persistent corneal ulceration where a corticosteroid has been used or is in use. Fungal culture should be taken when appropriate.

5.8 Topical Ophthalmic Use

DUREZOL is not indicated for intraocular administration.

5.9 Risk of Contamination

Do not allow the dropper tip to touch the eye, eyelids, or any surface, as this may contaminate the ophthalmic emulsion.

5.10 Contact Lens Wear

The anti-microbial preservative in DUREZOL may be absorbed by soft contact lenses. DUREZOL should not be instilled while wearing contact lenses. Remove contact lenses prior to instillation of DUREZOL. Contact lenses may be reinserted after 10 minutes following administration of DUREZOL.

6 ADVERSE REACTIONS

The following serious reactions are found elsewhere in the labeling:

- Intraocular Pressure (IOP) Increase [see Warnings and Precautions (5.1)]
- Cataracts [see Warnings and Precautions (5.2)]
- Delayed Healing [see Warnings and Precautions (5.3)]
- Corneal and Scleral Melting [see Warnings and Precautions (5.4)]
- Bacterial Infections [see Warnings and Precautions (5.5)]
- Viral Infections [see Warnings and Precautions (5.6)]
- Fungal Infections [see Warnings and Precautions (5.7)]

6.1 Ocular Surgery

Ocular adverse reactions occurring in 5% to 15% of subjects in clinical studies with DUREZOL, included corneal edema, ciliary and conjunctival hyperemia, eye pain, photophobia, posterior capsule opacification, anterior chamber cells, anterior chamber flare, conjunctival edema, and blepharitis. Other ocular adverse reactions occurring in 1% to 5% of subjects, included reduced visual acuity, punctate keratitis, eye inflammation, and iritis. Ocular adverse reactions occurring in less than 1% of subjects, included application-site discomfort or irritation, corneal pigmentation and striae, episcleritis, eye pruritus, eyelid irritation and crusting, foreign body sensation, increased lacrimation, macular edema, sclera hyperemia, and uveitis. Most of these reactions may have been the consequence of the surgical procedure.

6.2 Endogenous Anterior Uveitis

A total of 200 subjects participated in the clinical trials for endogenous anterior uveitis, of which 106 were exposed to DUREZOL. The most common adverse reactions of those exposed to DUREZOL occurring in 5% to 10% of subjects included blurred vision, eye irritation, eye pain, headache, increased IOP, iritis, limbal and conjunctival hyperemia, punctate keratitis, and uveitis. Adverse reactions occurring in 2% to 5% of subjects included anterior chamber flare, corneal edema, dry eye, iridocyclitis, photophobia, and reduced visual acuity.

8 USE IN SPECIFIC POPULATIONS

8.1 Pregnancy

Risk Summary

There are no available data on DUREZOL use in pregnant women to evaluate for a drug- associated risk of major birth defects, miscarriage or other adverse maternal or fetal outcomes.

Systemic exposure to DUREZOL following ocular administration is low [see Clinical Pharmacology (12.3)]. Consequently, the systemic exposure of a pregnant woman to difluprednate is expected to be minimal following topical ocular administration.

In animal reproductive studies, subcutaneous administration of difluprednate to pregnant rabbits and rats throughout organogenesis produced maternal toxicity, embryo-fetal toxicity and teratogenicity in rabbits and fetotoxicity in rats.

Administration of difluprednate to rats during late gestation through lactation did not produce adverse maternal, fetal or neonatal effects at clinically relevant doses.

The estimated background risk of major birth defects and miscarriage for the indicated population is unknown. All pregnancies have a background risk of birth defect, loss or other adverse outcomes. In the U.S. general population, the estimated background risk of major birth defects and miscarriage in clinically recognized pregnancies is 2% to 4% and 15% to 20%, respectively.

Data

Animal Data

In embryofetal development studies, subcutaneous administration of difluprednate to pregnant rats during the period of organogenesis decreased the placental weight, at doses greater than or equal to 10 mcg/kg/day (approximately 0.48-fold higher than the maximum recommended human ophthalmic dose [MRHOD] of 0.2 mg/day, on a mg/m^2 basis and assuming 100% absorption of the dose). Decreased weight gain and delayed ossification of the fetus were observed at a dose of 100 mcg/kg/day (approximately 4.8-fold higher than the MRHOD). The no-observed-effect level (NOEL) for teratogenic effects was 10 mcg/kg/day. In rabbits, subcutaneous administration of difluprednate during the period of organogenesis produced maternal toxicity, embryofetal lethality, fetal growth retardation and teratogenicity (cleft palate, cerebral hernia, exencephaly, hypogenesis of the first digit of the forelimbs, club hand, umbilical hernia and others) at 10 mcg/kg/day (approximately 0.97-fold the MRHOD on a mg/m^2 basis and assuming 100% absorption of the dose). The NOEL was 1 mcg/kg/day.

In a peri- or pre-/postnatal study in rats, subcutaneous administration of difluprednate during late gestation through lactation resulted in no abnormalities in postnatal development, growth and behavior or reproductive potential. The NOEL was greater than or equal to 10 mcg/kg/day (the highest dose tested; approximately 0.48-fold higher than the MRHOD on a mg/m^2basis and assuming 100% absorption of the dose).

8.2 Lactation

Risk Summary

There are no data on the presence of DUREZOL in human milk, the effects on the breastfed infants, or the effects on milk production to inform risk of DUREZOL to an infant during lactation. Systemically administered corticosteroids appear in human milk and could suppress growth, interfere with endogenous corticosteroid production, or cause other untoward effects. The systemic exposure of a breastfeeding woman to difluprednate is expected to be minimal following topical ocular administration, however, the possibility of harm to the breastfed child cannot be ruled out.

The developmental and health benefits of breastfeeding should be considered along with the mother’s clinical need for DUREZOL and any potential adverse effects on the breast-fed child from DUREZOL or from the underlying maternal condition.

8.3 Nursing Mothers

It is not known whether topical ophthalmic administration of corticosteroids could result in sufficient systemic absorption to produce detectable quantities in breast milk. Systemically administered corticosteroids appear in human milk and could suppress growth, interfere with endogenous corticosteroid production, or cause other untoward effects. Caution should be exercised when DUREZOL is administered to a nursing woman.

8.4 Pediatric Use

DUREZOL was evaluated in a 3-month multicenter, double-masked trial in 79 pediatric patients (39 DUREZOL; 40 prednisolone acetate) 0 to 3 years of age for the treatment of inflammation following cataract surgery. A similar safety profile was observed in pediatric patients comparing DUREZOL to prednisolone acetate ophthalmic suspension, 1%.

8.5 Geriatric Use

No overall differences in safety or effectiveness have been observed between elderly and younger patients.

11 DESCRIPTION

DUREZOL (difluprednate ophthalmic emulsion) 0.05% is a sterile, topical anti-inflammatory corticosteroid for topical ophthalmic use. The chemical name is 6α,9difluoro-11β,17,21-trihydroxypregna-1,4- diene-3,20-dione 21-acetate 17-butyrate (CAS number 23674-86-4). Difluprednate is represented by the following structural formula:

Difluprednate has a molecular weight of 508.56 g/mol, and the empirical formula is C27H34F2O7.

Each mL of DUREZOL contains: Active: difluprednate 0.5 mg (0.05%); Inactives: boric acid, castor oil, edetate disodium, glycerin, polysorbate 80, sodium acetate, sodium hydroxide (to adjust the pH to 5.2 to 5.8), water for injection. Preservative: sorbic acid 0.1%.

The emulsion is essentially isotonic with a tonicity of 304 to 411 mOsm/kg.

12 CLINICAL PHARMACOLOGY

12.1 Mechanism of Action

Corticosteroids inhibit the inflammatory response to a variety of inciting agents and may delay or slow healing. They inhibit edema, fibrin deposition, capillary dilation, leukocyte migration, capillary proliferation, fibroblast proliferation, deposition of collagen, and scar formation associated with inflammation. There is no generally accepted explanation for the mechanism of action of ocular corticosteroids. However, corticosteroids are thought to act by the induction of phospholipase A2 inhibitory proteins, collectively called lipocortins. It is postulated that these proteins control the biosynthesis of potent mediators of inflammation, such as prostaglandins and leukotreines by inhibiting the release of their common precursor arachidonic acid. Arachidonic acid is released from membrane phospholipids by phospholipase A2.

Difluprednate is structurally similar to other corticosteroids.

12.3 Pharmacokinetics

Difluprednate undergoes deacetylation in vivo to 6α, 9-difluoroprednisolone 17-butyrate (DFB), an active metabolite of difluprednate.

Clinical pharmacokinetic studies of difluprednate after repeat ocular instillation of 2 drops of difluprednate (0.01% or 0.05%) 4 times per day for 7 days showed that DFB levels in blood were below the quantification limit (50 ng/mL) at all time points for all subjects, indicating that the systemic absorption of difluprednate after ocular instillation of DUREZOL is limited.

13 NONCLINICAL TOXICOLOGY

13.1 Carcinogenesis, Mutagenesis, and Impairment of Fertility

Carcinogenesis

Long-term studies have not been conducted to evaluate the carcinogenic potential of difluprednate.

Mutagenesis

Difluprednate was not genotoxic in vitro in the Ames test, and in cultured mammalian cells (CHL/IU; a fibroblastic cell line derived from the lungs of newborn female Chinese hamsters) or in an in vivo micronucleus test of difluprednate in mice.

Impairment of Fertility

Treatment of male and female rats with subcutaneous difluprednate up to 10 mcg/kg/day prior to and during mating did not impair fertility in either gender.

13.2 Animal Toxicology and/or Pharmacology

In multiple studies performed in rodents and non-rodents, subchronic and chronic toxicity tests of difluprednate showed systemic effects, such as suppression of body weight gain; a decrease in lymphocyte count; atrophy of the lymphatic glands and adrenal gland; and for local effects, thinning of the skin; all of which were due to the pharmacologic action of the molecule and are well known glucocorticosteroid effects. Most, if not all of these effects were reversible after drug withdrawal. The NOEL for the subchronic and chronic toxicity tests were consistent between species and ranged from 1-1.25 mcg/kg/day.

14 CLINICAL STUDIES

14.1 Ocular Surgery

Clinical efficacy was evaluated in 2 randomized, double-masked, placebo-controlled trials in which subjects with an anterior chamber cell grade greater than or equal to "2" (a cell count of 11 or higher) after cataract surgery were assigned to DUREZOL or placebo (vehicle) following surgery. One drop of DUREZOL or vehicle was self-instilled either 2 times per day or 4 times per day for 14 days, beginning the day after surgery. The presence of complete clearing (a cell count of 0) was assessed 3, 8, and 15 days post surgery using a slit lamp binocular microscope. In the intent-to-treat analyses of both studies, a significant benefit was seen in the 4 times per day DUREZOL-treated group in ocular inflammation, at Days 8 and Day 15, and reduction of pain at Days 3, 8, and 15 when compared with placebo. The consolidated clinical trial results are provided below.

Figure 1 Percent of Subjects With Anterior Chamber Cells Clearing (Cell Count = 0)
Figure 2 Percent of Subjects Who Were Pain Free

14.2 Endogenous Anterior Uveitis

Clinical efficacy was evaluated in two randomized, double masked active controlled trials in which patients who presented with endogenous anterior uveitis were treated with either DUREZOL 4 times daily or prednisolone acetate ophthalmic suspension 1%, 8 times daily for 14 days. Both studies demonstrated that DUREZOL was equally effective as prednisolone acetate ophthalmic suspension 1% in treating subjects with endogenous anterior uveitis. The results are found in Table 1 below.

Table 1: Mean Change From Baseline in Anterior Chamber Cell Grade*
Study 1 Time Point | DUREZOL N = 57 | Prednisolone Acetate N = 53 | Difference† (95% CI)
Baseline | 2.6 | 2.5 | 0.0 (-0.22, 0.28)
Day 3 | -1.0 | -1.0 | -0.1 (-0.35, 0.25)
Day 7 | -1.6 | -1.5 | 0.0 (-0.31, 0.25)
Day 14 | -2.0 | -1.8 | -0.2 (-0.46, 0.10)
Day 21 | -2.2 | -1.9 | -0.3 (-0.53, 0.01)
Day 28 | -2.2 | -2.1 | -0.1 (-0.37, 0.18)
Day 35 | -2.1 | -2.0 | -0.1 (-0.39, 0.20)
Day 42 | -2.1 | -2.1 | 0.0 (-0.27, 0.34)
Study 2 Time Point | DUREZOL N = 50 | Prednisolone Acetate N = 40 | Difference† (95% CI)
Baseline | 2.4 | 2.4 | 0.0 (-0.21, 0.29)
Day 3 | -0.9 | -0.9 | 0.0 (-0.34, 0.25)
Day 7 | -1.7 | -1.6 | -0.1 (-0.35, 0.21)
Day 14 | -1.9 | -1.8 | -0.1 (-0.34, 0.20)
Day 21 | -2.0 | -2.0 | 0.0 (-0.25, 0.28)
Day 28 | -2.0 | -2.0 | 0.0 (-0.21, 0.26)
Day 35 | -2.1 | -2.0 | -0.1 (-0.32, 0.16)
Day 42 | -2.0 | -1.9 | -0.1 (-0.36, 0.24)
Abbreviation: CI, confidence interval.
*With 5 grades: 0 = 0 cells; 1 = 1 to 10 cells; 2 = 11 to 20 cells; 3 = 21 to 50 cells; and 4 = greater than 50 cells.
†Adjusted for baseline AC cell grade and study center and based on ITT dataset with LOCF for missing data.

16 HOW SUPPLIED/STORAGE AND HANDLING

DUREZOL (difluprednate ophthalmic emulsion) 0.05% is a sterile, aqueous topical ophthalmic emulsion supplied in an opaque plastic bottle with a controlled drop tip and a pink cap in the following sizes:

5 mL in a 8 mL bottle NDC 66758-086-75

Storage and Handling

Store at 20°C to 25°C (68°F to 77°F), excursions permitted between 15°C and 30°C (59°F and 86°F) [see USP Controlled Room Temperature]. Do not freeze. Protect from light. When not in use, keep the bottles in the protective carton. After opening, DUREZOL can be used until the expiration date on the bottle.

17 PATIENT COUNSELING INFORMATION

When to Consult a Physician

Advise patients to consult a physician if pain develops, or if redness, itching, or inflammation becomes aggravated [see Warnings and Precautions (5.5)].

Risk of Contamination

Advise patients to not allow the dropper tip to touch the eye, eyelids, or any surface, as this may contaminate the ophthalmic emulsion.

Contact Lens Wear

Advise patients to not use DUREZOL while wearing contact lenses. Advise patients to remove contact lenses prior to instillation of DUREZOL. Lenses may be reinserted after 10 minutes following administration of DUREZOL [see Warnings and Precautions (5.9)].

Manufactured by

Alcon Laboratories, Inc.

Fort Worth, Texas 76134 for

Sandoz Inc., Princeton, NJ 08540

xxxxxx

PRINCIPAL DISPLAY PANEL

NDC 66758-086-75

Rx Only

DUREZOL®

(difluprednate ophthalmic

emulsion) 0.05%

Sterile

5 mL

SANDOZ